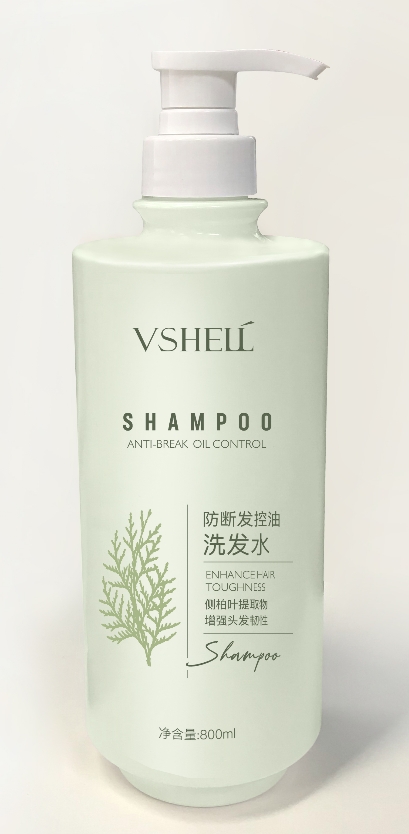 DRUG LABEL: Anti-dandruff lotion/shampoo
NDC: 84507-018 | Form: SHAMPOO
Manufacturer: Guangdong Miaolian Cosmetics Co., Ltd.
Category: otc | Type: HUMAN OTC DRUG LABEL
Date: 20240820

ACTIVE INGREDIENTS: SALICYLIC ACID 1.8 mg/100 mL
INACTIVE INGREDIENTS: WATER

PURPOSE

To help prevent recurrence of flaking and itching associated with dandruff

KEEP OUT OF REACH OF CHILDREN

In case of accidental ingestion, get medical help or contact a Poison Control Center immediately

INACTIVE INGREDIENT

water..

INDICATIONS AND USAGE

Helps prevent recurrence of flaking and itching associated with dandruff

WARNINGS

for external use only
when using this product avoid contact with eyes. if contact occurs, rinse eyes throughly with water.
stop use and ask a doctor if condition worsens or does not improve after regular use of this product as directed
keep out of reach of children
if swallowed, get medical help or contact poison control center immediately.

DOSAGE AND ADMINISTRATION

Apply the product to your hair and lather, wash for 15-20 seconds
Rinse thoroughly and dry